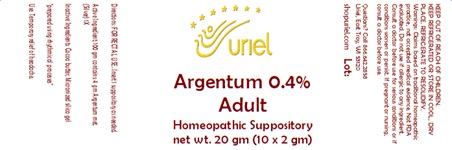 DRUG LABEL: Argentum 0.4%  Adult
NDC: 48951-1371 | Form: SUPPOSITORY
Manufacturer: Uriel Pharmacy Inc.
Category: homeopathic | Type: HUMAN OTC DRUG LABEL
Date: 20240130

ACTIVE INGREDIENTS: SILVER 1 [hp_X]/1 g
INACTIVE INGREDIENTS: COCOA BUTTER; SILICON DIOXIDE

Argentum 0.4% Adult

INDICATIONS AND USAGE

Directions: FOR RECTAL USE.

DOSAGE AND ADMINISTRATION

Insert 1 suppository as needed.

Active Ingredient: 100 gm contains:
4 gm Argentum met. (Silver) 1X

Inactive Ingredients: Cocoa butter, Micronized silica gel

"prepared using rhythmical processes"

PURPOSE

Use: Temporary relief of headache.

KEEP OUT OF REACH OF CHILDREN.

WARNINGS

Warnings: Claims based on traditional homeopathic practice, not accepted medical evidence. Not FDA evaluated. Do not use if allergic to any ingredient. Consult a doctor before use for serious conditions or if conditions worsen or persist. If pregnant or nursing, consult a doctor before use. Do not use if safety seals on box are broken or missing.

KEEP REFRIGERATED OR STORE IN COOL, DRY PLACE.

REFRIGERATE TO RESOLIDIFY.

QUESTIONS

Questions? Call 866.642.2858 Uriel, East Troy, WI 53120 shopuriel.com Lot: